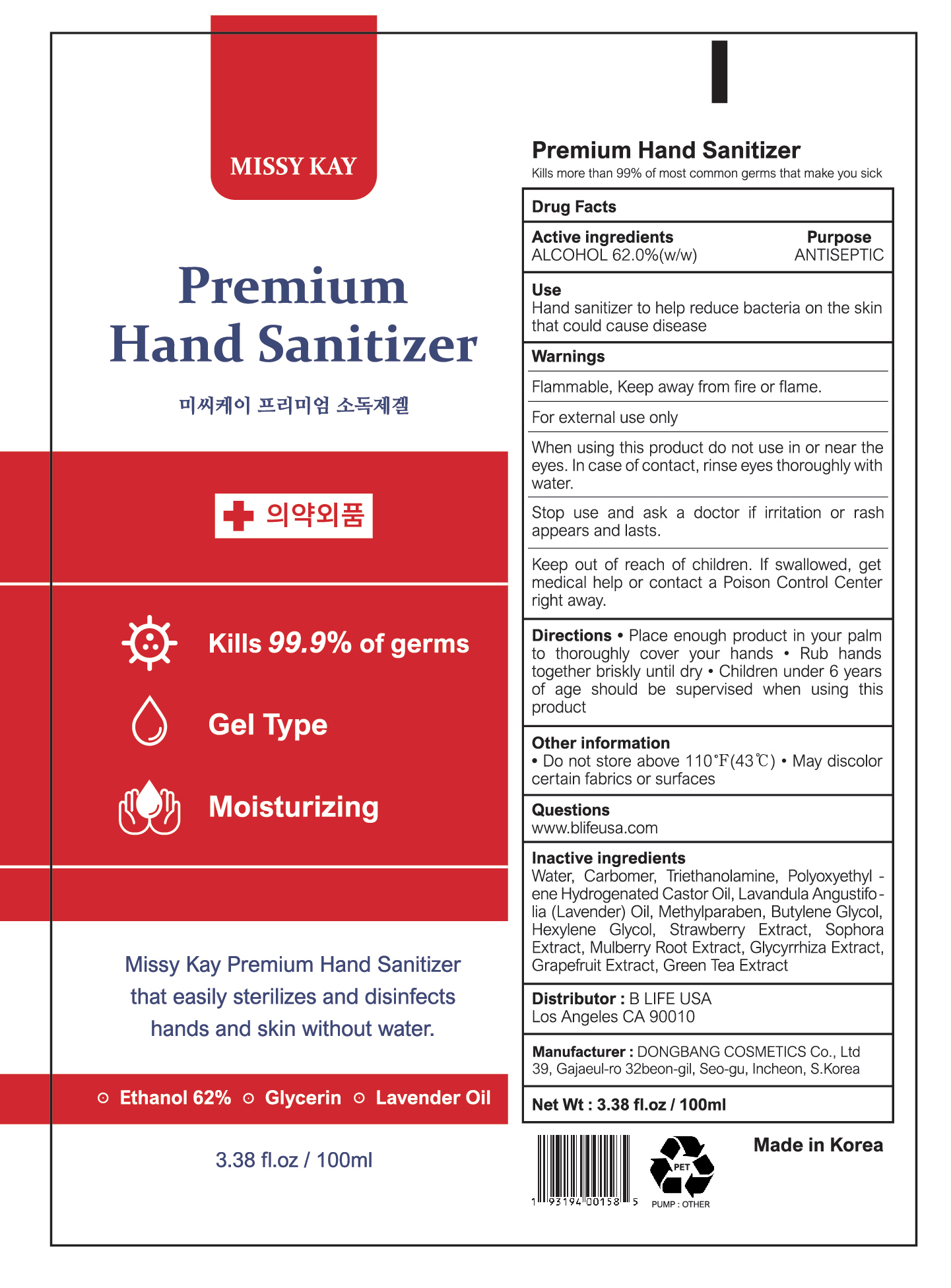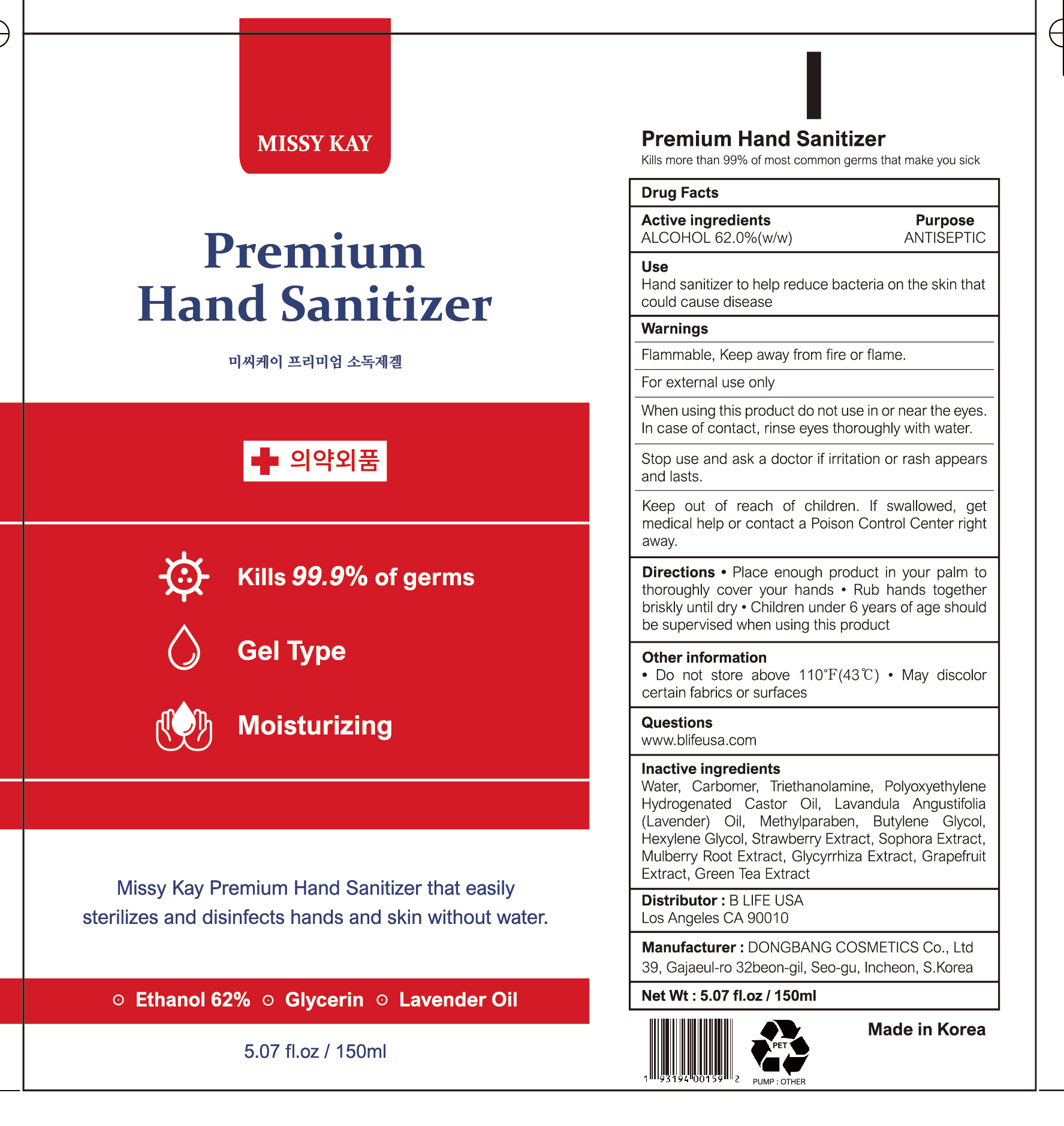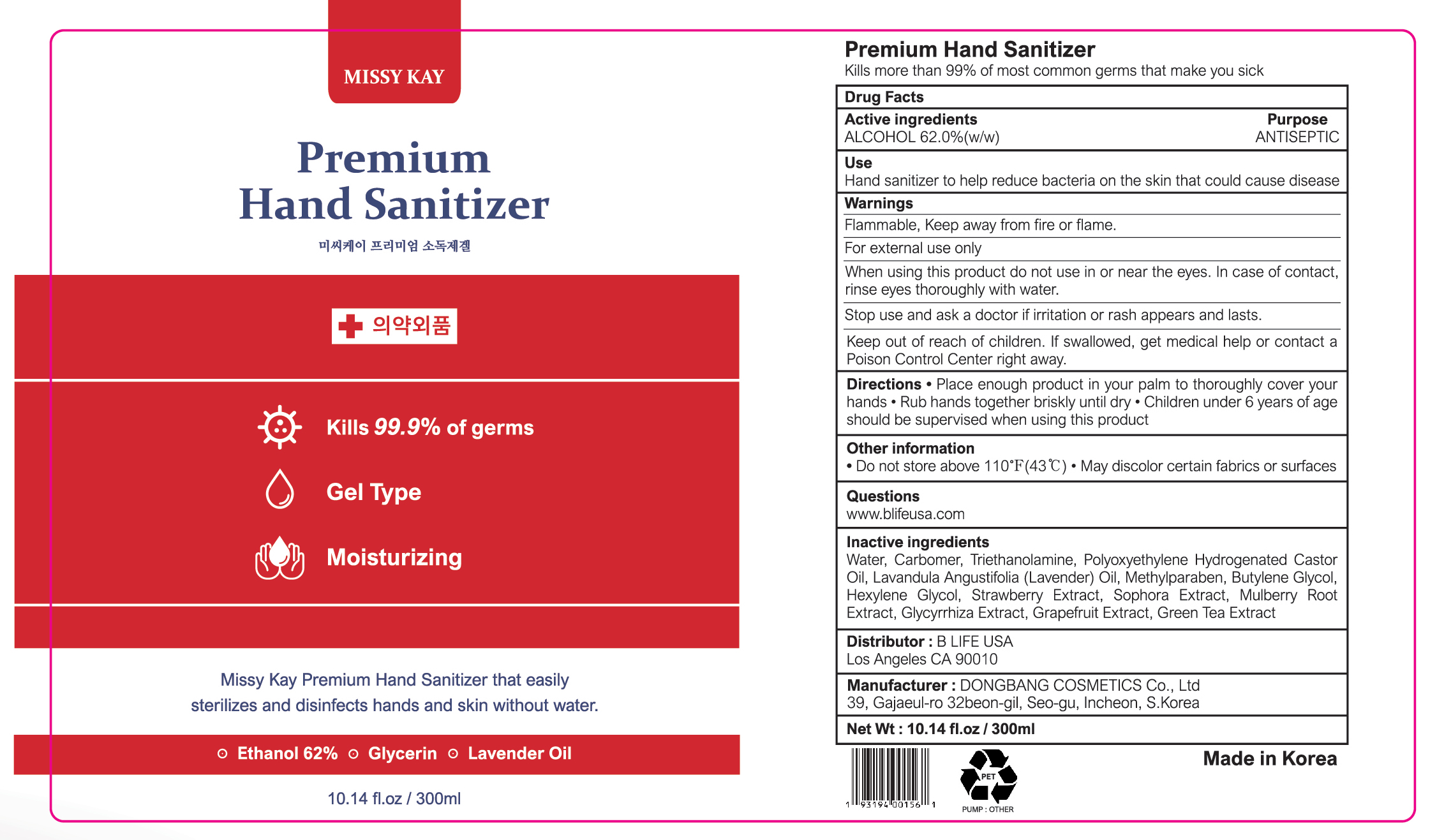 DRUG LABEL: MISSY KAY PREMIUM HAND SANITIZER
NDC: 75006-020 | Form: GEL
Manufacturer: BLIFE
Category: otc | Type: HUMAN OTC DRUG LABEL
Date: 20200428

ACTIVE INGREDIENTS: ALCOHOL 62 g/100 mL
INACTIVE INGREDIENTS: Water; CARBOMER HOMOPOLYMER, UNSPECIFIED TYPE; TROLAMINE; POLYETHYLENE GLYCOL, UNSPECIFIED; LAVENDER OIL; Methylparaben; Butylene Glycol; Hexylene Glycol

ACTIVE INGREDIENT

Active ingredients: 62.0%(w/w)

INACTIVE INGREDIENT

Inactive ingredients:

Water, Carbomer, Triethanolamine, Polyoxyethylene Hydrogenated Castor Oil, Lavandula Angustifolia (Lavender) Oil, Methylparaben, Butylene Glycol, Hexylene Glycol, Strawberry Extract, Sophora Extract, Mulberry Root Extract, Glycyrrhiza Extract, Grapefruit Extract, Green Tea Extract

PURPOSE

Purpose: ANTISEPTIC

WARNINGS

■ Flammable. Keep away from fire or flame.
■ For external use only
■ When using this product do not use in or near the eyes. In case of contact, rinse eyes thoroughly with water.
■ Stop use and ask a doctor if irritation or rash appears and lasts
■ Keep out of reach of children. If swallowed, get medical help or contact a Poison Control Center right away.

Keep out of reach of children. If swallowed, get medical help or contact a Poison Control Center right away.

Uses

Hand sanitizer to help reduce bacteria on the skin that could cause disease

Directions

■ Place enough product in your palm to thoroughly cover your hands
■ Rub hands together briskly until dry
■ Children under 6 years of age should be supervised when using this product

Other Information

■ Do not store above 110℉(43℃)
■ May discolor certain fabrics or surfaces

Questions

www.blifeusa.com